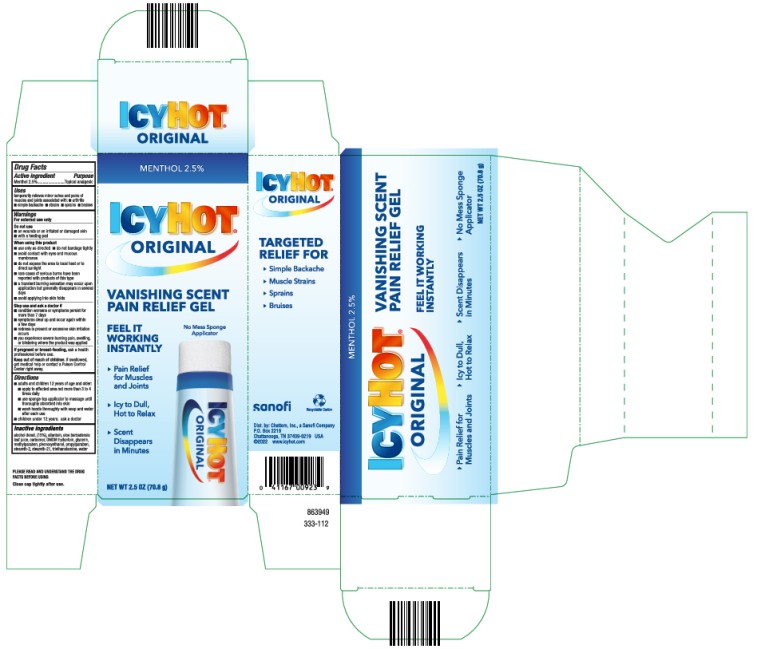 DRUG LABEL: Icy Hot Vanishing Scent
NDC: 41167-0092 | Form: GEL
Manufacturer: Chattem, Inc.
Category: otc | Type: HUMAN OTC DRUG LABEL
Date: 20220929

ACTIVE INGREDIENTS: MENTHOL 0.025 g/1 g
INACTIVE INGREDIENTS: ALCOHOL; ALLANTOIN; ALOE VERA LEAF; CARBOMER HOMOPOLYMER, UNSPECIFIED TYPE; DMDM HYDANTOIN; GLYCERIN; METHYLPARABEN; PHENOXYETHANOL; PROPYLPARABEN; STEARETH-2; STEARETH-21; TROLAMINE; WATER

Icy Hot Vanishing Scent

Drug Facts

Active ingredient

Menthol 2.5%

Purpose

Topical analgesic

Uses

temporarily relieves minor aches and pains of muscles and joints associated with:

- arthritis
- simple backache
- strains
- sprains
- bruises

Warnings

For external use only

Do not use

■ on wounds or on irritated or damaged skin

■ with a heating pad

When using this product

■ use only as directed

■ do not bandage tightly

■ avoid contact with eyes and mucous membranes

■ do not expose the area to local heat or to direct sunlight

■ rare cases of serious burns have been reported with products of this type

■ a transient burning sensation may occur upon application but generally disappears in several days

■ avoid applying into skin folds

Stop use and ask a doctor if

■ condition worsens or symptoms persist for more than 7 days

■ symptoms clear up and occur again within a few days

■ redness is present or excessive skin irritation occurs

■ you experience severe burning pain, swelling, or blistering where the product was applied

If pregnant or breast-feeding,

ask a health professional before use

Keep out of reach of children.

If swallowed, get medical help or contact a Poison Control Center right away.

Directions

■ adults and children 12 years of age and older:

■ apply to affected area not more than 3 to 4 times daily

■ use sponge-top applicator to massage until thoroughly absorbed into skin

■ wash hands thoroughly with soap and water after each use

■ children under 12 years: ask a doctor

Inactive ingredients

alcohol denat. (15%), allantoin, aloe barbadensis leaf juice, carbomer, DMDM hydantoin, glycerin, methylparaben, phenoxyethanol, propylparaben, steareth-2, steareth-21, triethanolamine, water

Keep carton as it contains important information.

Close cap tightly after use.

PRINCIPAL DISPLAY PANEL

MENTHOL 2.5%
NEW LOOK
ICYHOT®
ORIGINAL
VANISHING SCENT
PAIN RELIEVING GEL
Net wt 2.5 oz (70.8 g)